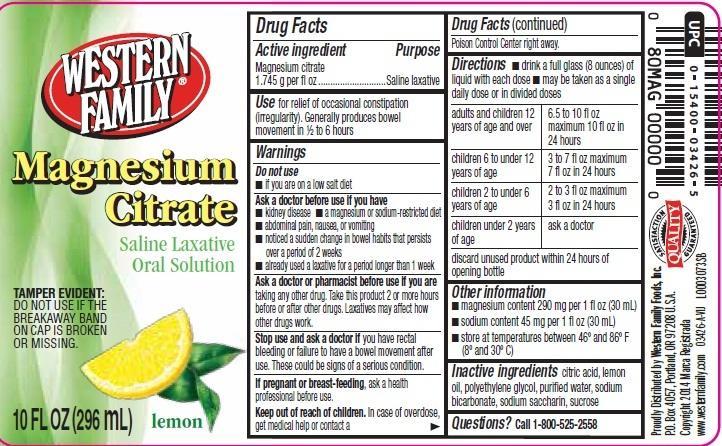 DRUG LABEL: Citroma
NDC: 55312-667 | Form: LIQUID
Manufacturer: Western Family Foods, Inc
Category: otc | Type: HUMAN OTC DRUG LABEL
Date: 20250220

ACTIVE INGREDIENTS: MAGNESIUM CITRATE 17.45 mg/1 mL
INACTIVE INGREDIENTS: CITRIC ACID MONOHYDRATE; LEMON OIL; POLYETHYLENE GLYCOL, UNSPECIFIED; WATER; SODIUM BICARBONATE; SACCHARIN SODIUM; SUCROSE

Western Family 667
Citrus Citrate

Active Ingredient

Magnesium citrate 1.745 g per fl oz

Purpose

Saline Laxative

Use

for relief of occasional constipation (irregularity). Generally produces bowel movement in 1/2 to 6 hours

Warnings

Do not use

- if you are on a low salt diet

Ask a doctor

before use if you have

- kidney disease
- a magnesium or sodium-restricted diet
- abdominal pain, nausea or vomiting
- noticed a sudden change in bowel habits that persists over a period of 2 weeks
- already use a laxative for a period longer than 1 week

Ask a doctor or pharmacist before use if you are

taking any other drugs. Take this product 2 or more hours before or after other drugs. Laxatives may affect how other drugs work.

Stop Use and ask a doctor if

you have rectal bleeding or failure to have a bowel moverment after use. These could be signs of a serious condition.

If pregnant or breast-feeding

ask a health professional before use.

Keep out of reach of children

In case of overdose, get medical help or contact a Poison Control Center right away.

Directions

- drink a full glass (8 ounces) of liquid with each dose
- may be taken as a single daily dose or in divided doses

adults and children 12 years of age and over - 6.5 to 10 fl oz maximum 10 fl oz in 24 hours

children 6 to under 12 years of age - 3 to 7 fl oz maximum 7 fl oz in 24 hours

children 2 to under 6 years of age - 2 to 3 fl oz maximum 3 fl oz in 24 hours

children under 2 years of age - ask a doctor

discard unused product within 24 hours of opening bottle

Other information

- magnesium content 290 mg per 1 fl oz (30 mL)
- sodium content 45 mg per 1 fl oz (30 mL)
- store at temperatures between 46º and 86º F (8º and 30º C)

Inactive ingredients

citric acid, lemon oil, polyethylene glycol, purified water, sodium bicarbonate, sodium saccharin, sucrose

Questions or comments

1-800-525-2558

Adverse Reactions

Proudly Distribted by Western Family Foods, Inc.

P.O.Box 4057, Portland, OR 97208 U.S.A.

Copyright 2014 Marca Registrada

www. westernfamily.com

Principal Display Panel

WESTERN

FAMILY

Magnesium

Citrate

Saline Laxatixe

Oral Solution

TAMPER EVIDENT:

DO NOT USE IF THE BREAKAWAY BAND ON CAP IS BROKEN OR MISSING.

10 FL OZ (296 mL)